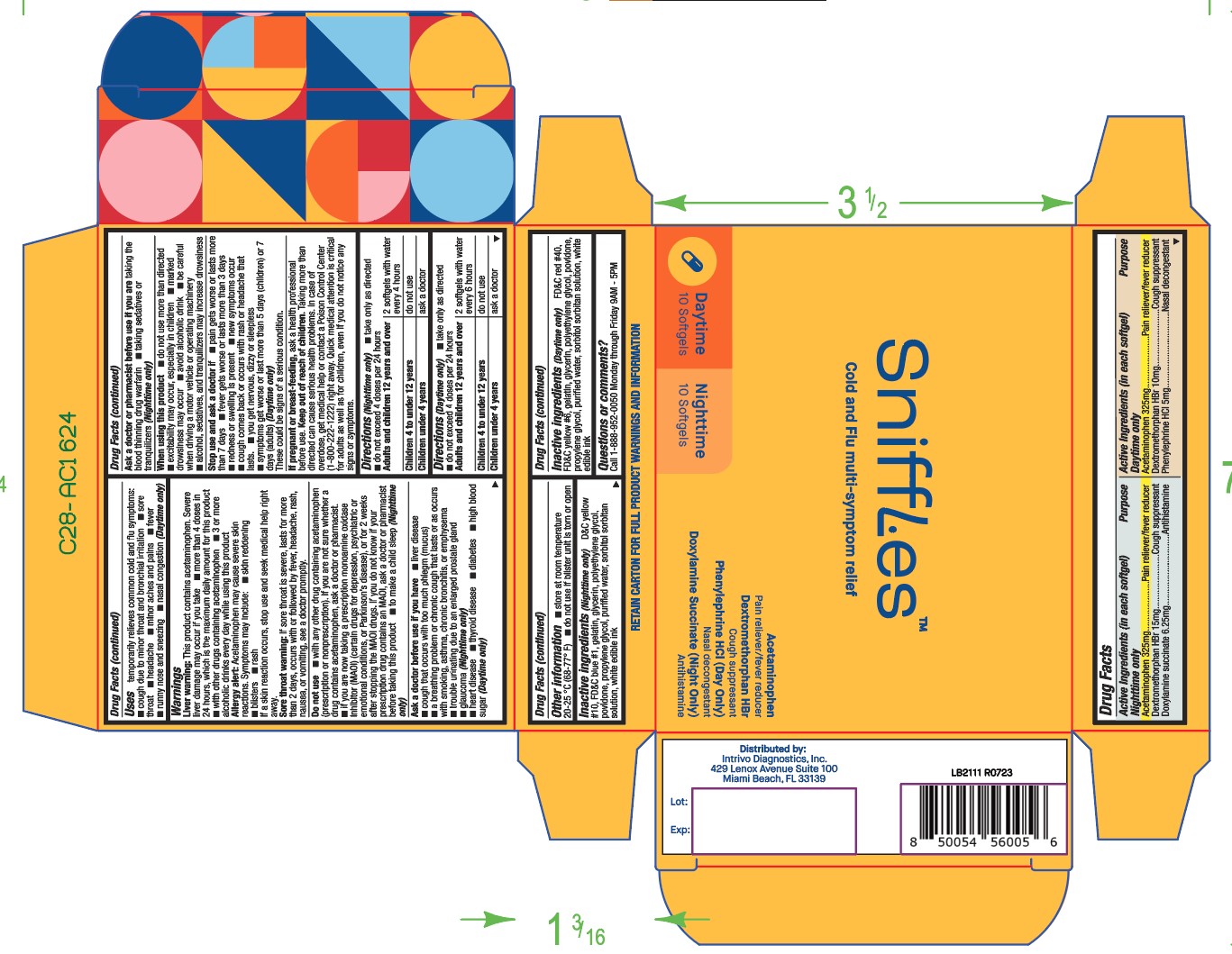 DRUG LABEL: Day and Night Multi Symptom Cold and Flu Relief
NDC: 83558-020 | Form: KIT | Route: ORAL
Manufacturer: Intrivo Diagnostics Inc.
Category: otc | Type: HUMAN OTC DRUG LABEL
Date: 20231013

ACTIVE INGREDIENTS: ACETAMINOPHEN 325 mg/1 1; DEXTROMETHORPHAN HYDROBROMIDE 10 mg/1 1; PHENYLEPHRINE HYDROCHLORIDE 5 mg/1 1; ACETAMINOPHEN 325 mg/1 1; DEXTROMETHORPHAN HYDROBROMIDE 15 mg/1 1; DOXYLAMINE SUCCINATE 6.25 mg/1 1
INACTIVE INGREDIENTS: FD&C RED NO. 40; FD&C YELLOW NO. 6; GELATIN; GLYCERIN; POLYETHYLENE GLYCOL, UNSPECIFIED; POVIDONE; PROPYLENE GLYCOL; WATER; SORBITOL SOLUTION; D&C YELLOW NO. 10; FD&C BLUE NO. 1; GELATIN; GLYCERIN; POLYETHYLENE GLYCOL, UNSPECIFIED; POVIDONE; PROPYLENE GLYCOL; WATER; SORBITOL SOLUTION

Day and Night Multi Symptom Cold and Flu Relief

Active ingredient(s)

Active Ingredients (in each softgel)
Nighttime only
Acetaminophen 325mg
Dextromethorphan HBr 15mg
Doxylamine succinate 6.25mg

Active Ingredients (in each softgel)
Daytime only
Acetaminophen 325mg
Dextromethorphan HBr 10mg

Phenylephrine HCl 5mg

Purpose

Nighttime only
Pain reliever/fever reducer
Cough suppressant
Antihistamine

Daytime only
Pain reliever/fever reducer
Cough suppressant
Nasal decongestant

Use(s)

temporarily relieves common cold and flu symptoms:

- cough due to minor throat and bronchial irritation
- sore throat
- headache
- minor aches and pains
- fever
- runny nose and sneezing
- nasal congestion (Daytime only)

Warnings

Liver warning: This product contains acetaminophen. Severe liver damage may occur if you take

- more than 4 doses in 24 hours, which is the maximum daily amount for this product
- with other drugs containing acetaminophen
- 3 or more alcoholic drinks every day while using this product

Allergy alert: Acetaminophen may cause severe skin
reactions. Symptoms may include:

- skin reddening
- blisters
- rash

If a skin reaction occurs, stop use and seek medical help right
away.

Sore throat warning: If sore throat is severe, lasts for more
than 2 days, occurs with or followed by fever, headache, rash,
nausea, or vomiting, see a doctor promptly.

Do not use

- with any other drug containing acetaminophen
  (prescription or nonprescription). If you are not sure whether a
  drug contains acetaminophen, ask a doctor or pharmacist.

- if you are now taking a prescription monoamine oxidase
  inhibitor (MAOI) (certain drugs for depression, psychiatric or
  emotional conditions, or Parkinson’s disease), or for 2 weeks
  after stopping the MAOI drugs. If you do not know if your
  prescription drug contains an MAOI, ask a doctor or pharmacist
  before taking this product
- to make a child sleep (Nighttime only)

Ask a doctor before use if

- liver disease
- cough that occurs with too much phlegm (mucus)
- a breathing problem or chronic cough that lasts or as occurs with smoking, asthma, chronic bronchitis, or emphysema
- trouble urinating due to an enlarged prostate gland
- glaucoma (Nighttime only)
- heart disease
- thyroid disease
- diabetes high blood sugar (Daytime only)

Ask a doctor or pharmacist before use if

you are taking the blood thinning drug warfarin

- taking sedatives or tranquilizers (Nighttime only)

When using this product

- do not use more than directed
- excitability may occur, especially in children
- marked drowsiness may occur
- avoid alcoholic drink
- be careful when driving a motor vehicle or operating machinery
- alcohol, sedatives, and tranquilizers may increase drowsiness

Stop use and ask a doctor if

- pain gets worse or lasts more than 7 days
- fever gets worse or lasts more than 3 days
- redness or swelling is present
- new symptoms occur
- cough comes back or occurs with rash or headache that lasts.
- you get nervous, dizzy or sleepless
- symptoms get worse or last more than 5 days (children) or 7 days (adults) (Daytime only)
  These could be signs of a serious condition.

If pregnant or breastfeeding,

ask a health professional before use.

Keep out of reach of children

Taking more than directed can cause serious health problems. In case of overdose, get medical help or contact a Poison Control Center

(1-800-222-1222) right away. Quick medical attention is critical for adults as well as for children, even if you do not notice any signs or symptoms.

Directions

Directions (Nighttime only)

- take only as directed
- do not exceed 4 doses per 24 hours
  Adults and children 12 years and over: 2 softgels with water every 4 hours
  Children 4 to under 12 years: do not use
  Children under 4 years: ask a doctor

Directions (Daytime only)

- take only as directed
- do not exceed 4 doses per 24 hours
  Adults and children 12 years and over: 2 softgels with water every 6 hours
  Children 4 to under 12 years: do not use
  Children under 4 years: ask a doctor

Other information

- store at room temperature 20-25 °C (68-77° F)
- do not use if blister unit is torn or open

Inactive ingredients

Inactive ingredients (Nighttime only)

D&C yellow #10, FD&C blue #1, gelatin, glycerin, polyethylene glycol,
povidone, propylene glycol, purified water, sorbitol sorbitan
solution, white edible ink

Inactive ingredients (Daytime only)

FD&C red #40, FD&C yellow #6, gelatin, glycerin, polyethylene glycol, povidone,
propylene glycol, purified water, sorbitol sorbitan solution, white
edible ink

Questions/Comments

Call 1-888-952-0050 Monday through Friday 9AM - 5PM

Principal Display Panel

Daytime and Nighttime softgels